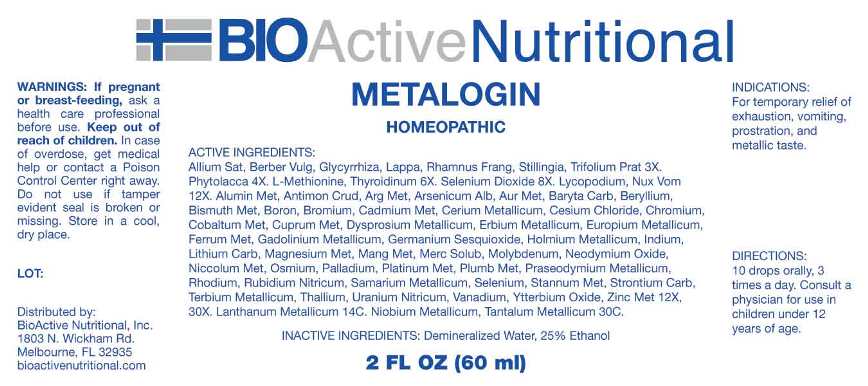 DRUG LABEL: Metalogin
NDC: 43857-0617 | Form: LIQUID
Manufacturer: BioActive Nutritional, Inc.
Category: homeopathic | Type: HUMAN OTC DRUG LABEL
Date: 20231117

ACTIVE INGREDIENTS: GARLIC 3 [hp_X]/1 mL; BERBERIS VULGARIS ROOT BARK 3 [hp_X]/1 mL; GLYCYRRHIZA GLABRA 3 [hp_X]/1 mL; ARCTIUM LAPPA ROOT 3 [hp_X]/1 mL; FRANGULA ALNUS BARK 3 [hp_X]/1 mL; STILLINGIA SYLVATICA ROOT 3 [hp_X]/1 mL; TRIFOLIUM PRATENSE FLOWER 3 [hp_X]/1 mL; PHYTOLACCA AMERICANA ROOT 4 [hp_X]/1 mL; METHIONINE 6 [hp_X]/1 mL; THYROID 6 [hp_X]/1 mL; SELENIUM DIOXIDE 8 [hp_X]/1 mL; LYCOPODIUM CLAVATUM SPORE 12 [hp_X]/1 mL; STRYCHNOS NUX-VOMICA SEED 12 [hp_X]/1 mL; ALUMINUM 12 [hp_X]/1 mL; ANTIMONY TRISULFIDE 12 [hp_X]/1 mL; SILVER 12 [hp_X]/1 mL; ARSENIC TRIOXIDE 12 [hp_X]/1 mL; GOLD 12 [hp_X]/1 mL; BARIUM CARBONATE 12 [hp_X]/1 mL; BERYLLIUM 12 [hp_X]/1 mL; BISMUTH 12 [hp_X]/1 mL; BORON 12 [hp_X]/1 mL; BROMINE 12 [hp_X]/1 mL; CADMIUM 12 [hp_X]/1 mL; CERIUM 12 [hp_X]/1 mL; CESIUM CHLORIDE 12 [hp_X]/1 mL; CHROMIUM 12 [hp_X]/1 mL; COBALT 12 [hp_X]/1 mL; COPPER 12 [hp_X]/1 mL; DYSPROSIUM 12 [hp_X]/1 mL; ERBIUM 12 [hp_X]/1 mL; EUROPIUM 12 [hp_X]/1 mL; IRON 12 [hp_X]/1 mL; GADOLINIUM 12 [hp_X]/1 mL; GERMANIUM SESQUIOXIDE 12 [hp_X]/1 mL; HOLMIUM 12 [hp_X]/1 mL; INDIUM 12 [hp_X]/1 mL; LITHIUM CARBONATE 12 [hp_X]/1 mL; MAGNESIUM 12 [hp_X]/1 mL; MANGANESE 12 [hp_X]/1 mL; MERCURIUS SOLUBILIS 12 [hp_X]/1 mL; MOLYBDENUM 12 [hp_X]/1 mL; NEODYMIUM OXIDE 12 [hp_X]/1 mL; NICKEL 12 [hp_X]/1 mL; OSMIUM 12 [hp_X]/1 mL; PALLADIUM 12 [hp_X]/1 mL; PLATINUM 12 [hp_X]/1 mL; LEAD 12 [hp_X]/1 mL; PRASEODYMIUM 12 [hp_X]/1 mL; RHODIUM 12 [hp_X]/1 mL; RUBIDIUM NITRITE 12 [hp_X]/1 mL; SAMARIUM 12 [hp_X]/1 mL; SELENIUM 12 [hp_X]/1 mL; TIN 12 [hp_X]/1 mL; STRONTIUM CARBONATE 12 [hp_X]/1 mL; TERBIUM 12 [hp_X]/1 mL; THALLIUM 12 [hp_X]/1 mL; URANYL NITRATE HEXAHYDRATE 12 [hp_X]/1 mL; VANADIUM 12 [hp_X]/1 mL; YTTERBIUM OXIDE 12 [hp_X]/1 mL; ZINC 12 [hp_X]/1 mL; LANTHANUM 14 [hp_C]/1 mL; NIOBIUM 30 [hp_C]/1 mL; TANTALUM 30 [hp_C]/1 mL
INACTIVE INGREDIENTS: WATER; ALCOHOL

DRUG FACTS:

ACTIVE INGREDIENTS:

Allium Sativum 3X, Berberis Vulgaris 3X, Glycyrrhiza Glabra 3X, Lappa Major 3X, Rhamnus Frangula 3X, Stillingia Sylvatica 3X, Trifolium Pratense 3X, Phytolacca Decandra 3X, L-Methionine 6X, Thyroidinum (Suis) 6X, Selenium Dioxide 8X, Lycopodium Clavatum 12X, Nux Vomica 12X, Aluminum Metallicum 12X, 30X, Antimonium Crudum 12X, 30X, Argentum Metallicum 12X, 30X, Arsenicum Album 12X, 30X, Aurum Metallicum 12X, 30X, Baryta Carbonica 12X, 30X, Beryllium Metallicum 12X, 30X, Bismuthum Metallicum 12X, 30X, Boron 12X, 30X, Bromium 12X, 30X, Cadmium Metallicum 12X, 30X, Cerium Metallicum 12X, 30X, Cesium Chloride 12X, 30X, Chromium 12X, 30X, Cobaltum Metallicum 12X, 30X, Cuprum Metallicum 12X, 30X, Dysprosium Metallicum 12X, 30X, Erbium Metallicum 12X, 30X, Europium Metallicum 12X, 30X, Ferrum Metallicum 12X, 30X, Gadolinium Metallicum 12X, 30X, Germanium Sesquioxide 12X, 30X, Holmium Metallicum 12X, 30X, Indium Metallicum 12X, 30X, Lithium Carbonicum 12X, 30X, Magnesium Metallicum 12X, 30X, Manganum Metallicum 12X, 30X, Mercurius Solubilis 12X, 30X, Molybdenum 12X, 30X, Neodymium Oxide 12X, 30X, Niccolum Metallicum 12X, 30X, Osmium Metallicum 12X, 30X, Palladium Metallicum 12X, 30X, Platinum Metallicum 12X, 30X, Plumbum Metallicum 12X, 30X, Praseodymium Metallicum 12X, 30X, Rhodium Metallicum 12X, 30X, Rubidium Nitricum 12X, 30X, Samarium Metallicum 12X, 30X, Selenium Metallicum 12X, 30X, Stannum Metallicum 12X, 30X, Strontium Carbonicum 12X, 30X, Terbium Metallicum 12X, 30X, Thallium Metallicum 12X, 30X, Uranium Nitricum 12X, 30X, Vanadium Metallicum 12X, 30X, Ytterbium Oxide 12X, 30X, Zincum Metallicum 12X, 30X, Lanthanum Metallicum 14C, Niobium Metallicum 30C, Tantalum Metallicum 30C.

INDICATIONS:

For temporary relief of exhaustion, vomiting, prostration, and metallic taste.

WARNINGS:

If pregnant or breast-feeding, ask a health care professional before use.

Keep out of reach of children. In case of overdose, get medical help or contact a Poison Control Center right away.

Do not use if tamper evident seal is broken or missing.

Store in cool, dry place.

Keep out of reach of children. In case of overdose, get medical help or contact a Poison Control Center right away.

DIRECTIONS:

10 drops orally, 3 times a day. Consult a physician for use in children under 12 years of age.

INDICATIONS:

For temporary relief of exhaustion, vomiting, prostration, and metallic taste.

INACTIVE INGREDIENTS:

Demineralized Water, 25% Ethanol

QUESTIONS:

Distributed by:
BioActive Nutritional, Inc.
1803 N. Wickham Rd.
Melbourne, FL 32935
bioactivenutritional.com

PACKAGE LABEL DISPLAY:

BIOActive Nutritional

METALOGIN

HOMEOPATHIC

2 FL OZ (60 ml)